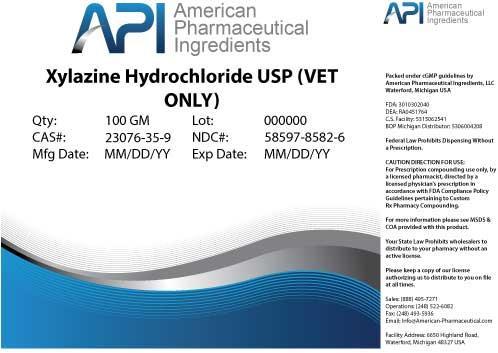 DRUG LABEL: Xylazine Hydrochloride
NDC: 58597-8582 | Form: POWDER
Manufacturer: AMERICAN PHARMACEUTICAL INGREDIENTS LLC
Category: other | Type: BULK INGREDIENT
Date: 20140502

ACTIVE INGREDIENTS: Xylazine Hydrochloride 1 g/1 g

Xylazine Hydrochloride